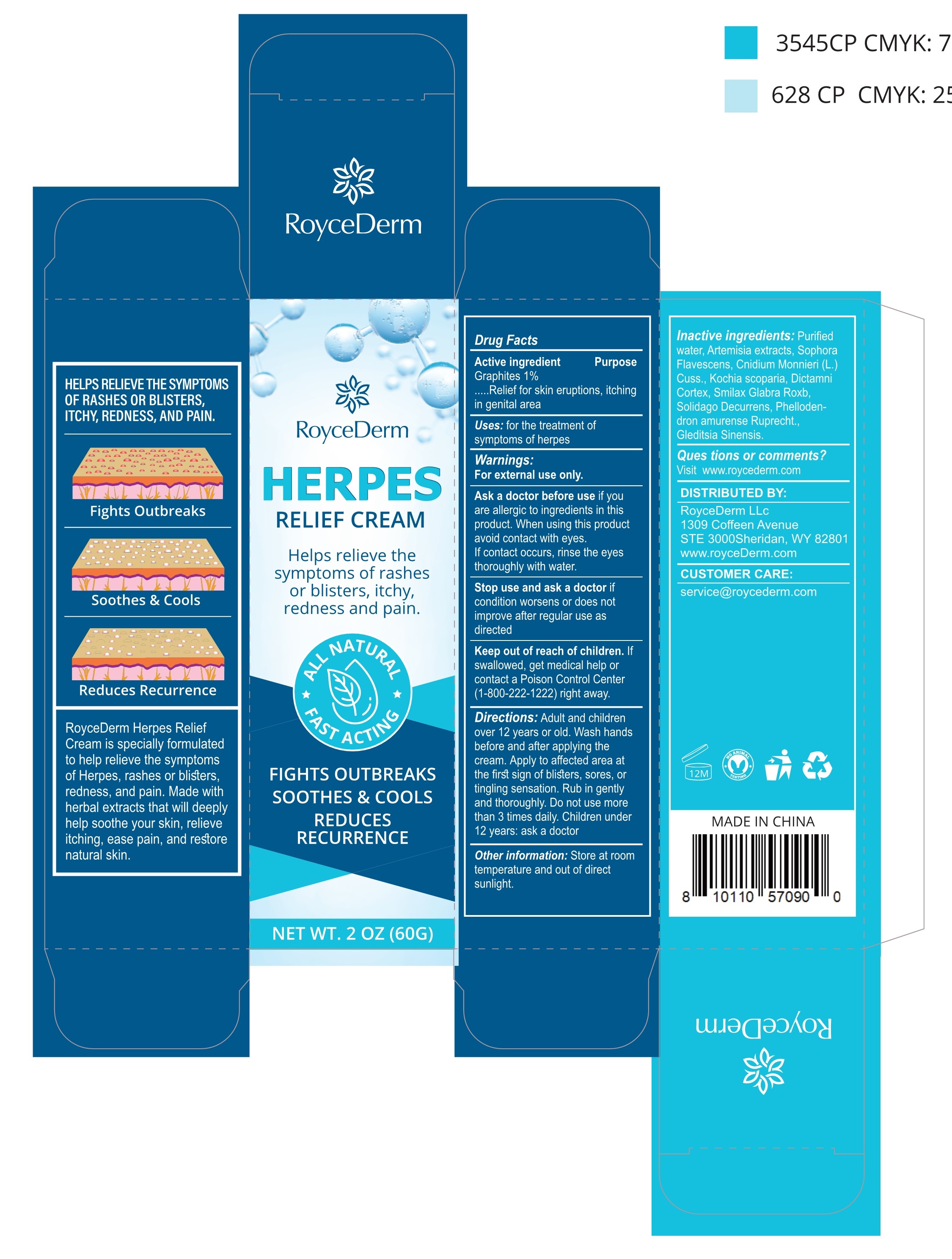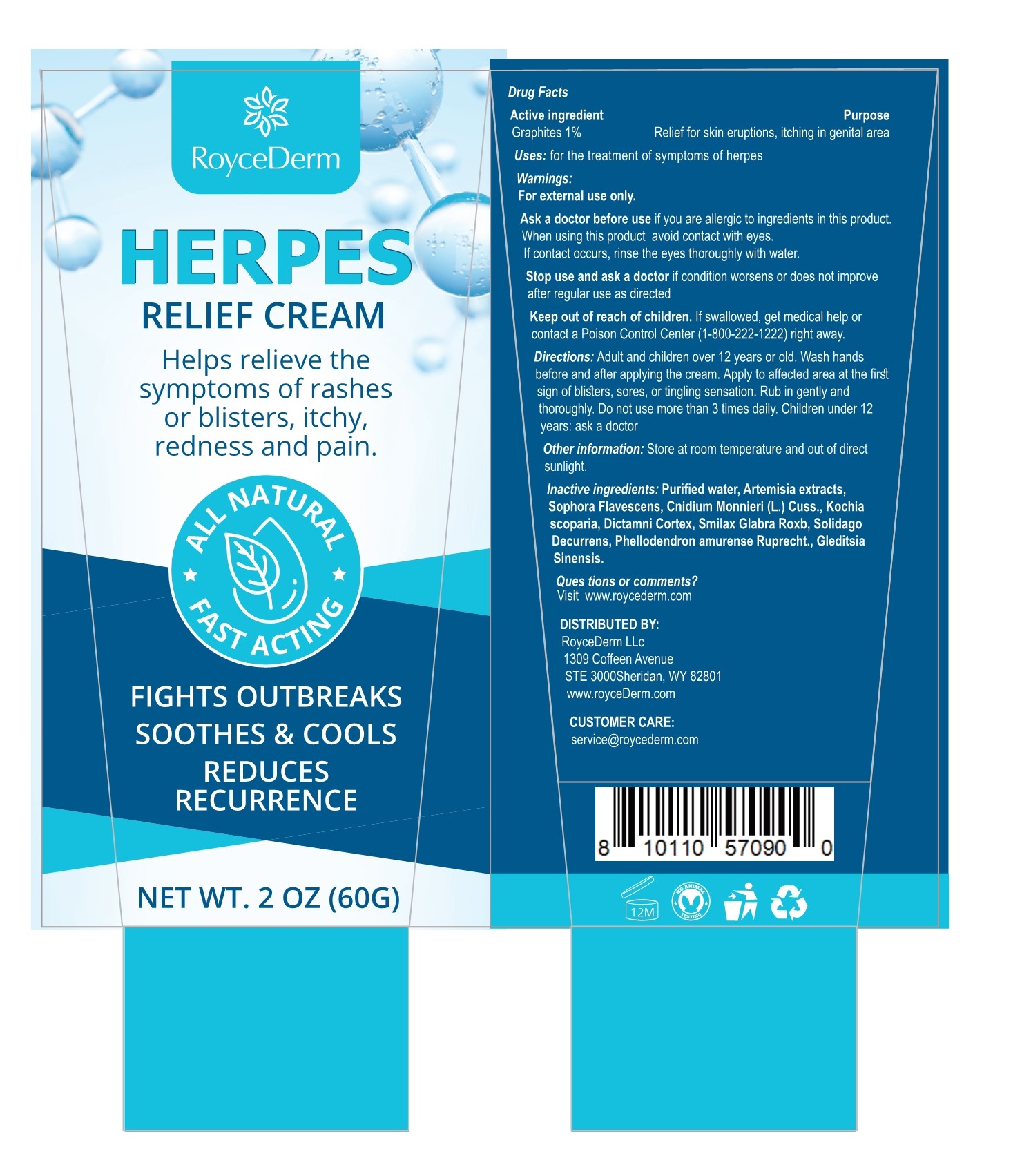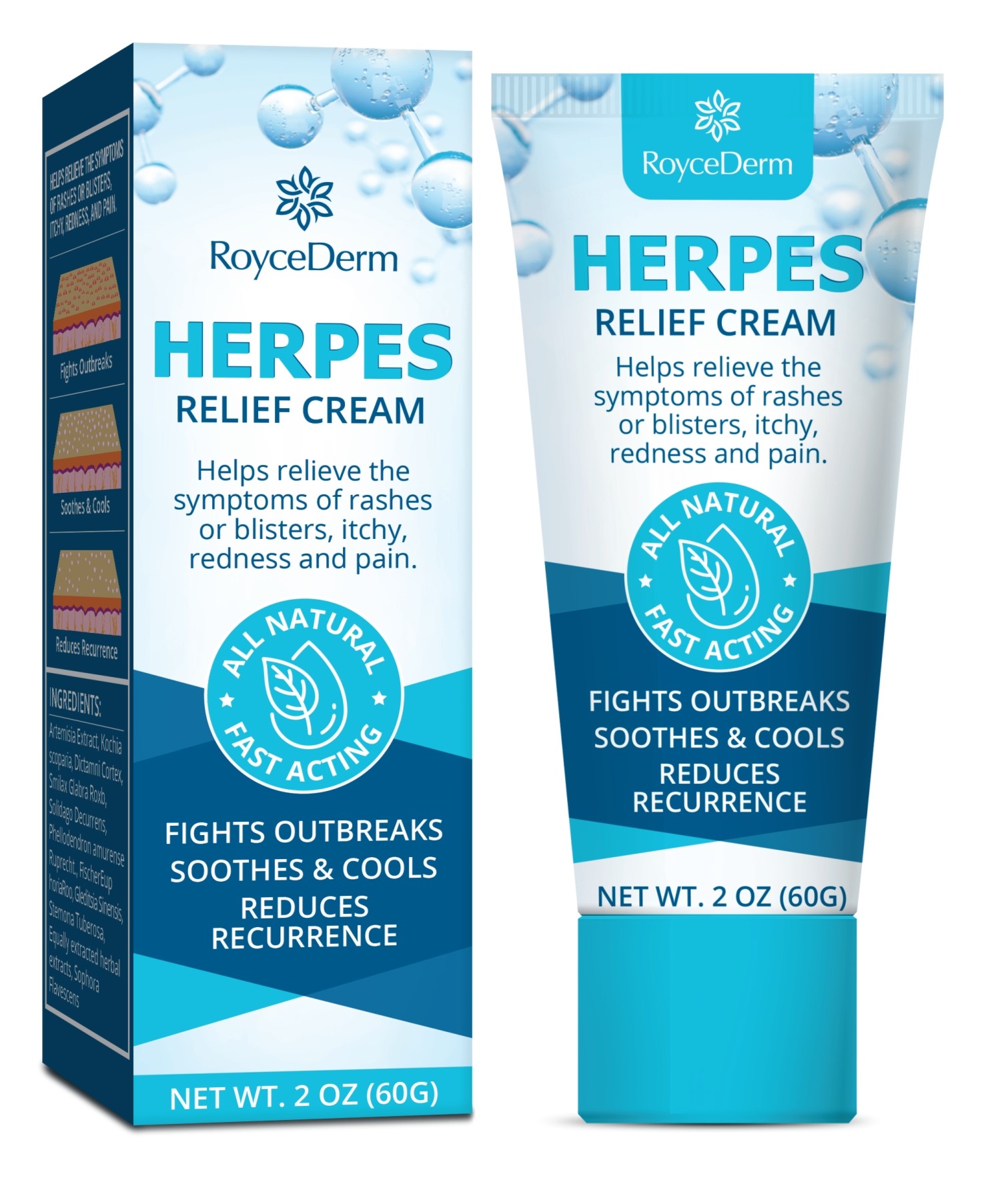 DRUG LABEL: Herpes Relief Cream
NDC: 81799-005 | Form: CREAM
Manufacturer: Ehy Holdings LLC
Category: otc | Type: HUMAN OTC DRUG LABEL
Date: 20230111

ACTIVE INGREDIENTS: GRAPHITE 1 g/100 g
INACTIVE INGREDIENTS: DICTAMNUS DASYCARPUS ROOT; WATER; WORMWOOD; SMILAX GLABRA WHOLE; CNIDIUM MONNIERI FRUIT; BASSIA SCOPARIA POLLEN; SOPHORA FLAVESCENS ROOT

81799-005
Herpes Relief Cream

Active Ingredient(s)

Graphites 1%

Purpose

Relief for skin eruptions, itchingin genital area

Use

for the treatment ofsymptoms of herpes

Warnings

For external use only

Do not use morethan 3 times daily. Children under12 years: ask a docto

WHEN USING

When using this productavoid contact with eyes.lf contact occurs, rinse the eyesthoroughly with water.

Stop use and ask a doctor if condition worsens or does not improve

KEEP OUT OF REACH OF CHILDREN

contact a Poison Control Center (1-800-222-1222) right away.

Directions

Adult and children over 12 vears or old. Wash handsbefore and after applying the cream. Apply to affected area at the firstsign of blisters, sores, or tingling sensation. Rub in gently andthoroughly. Do not use more than 3 times daily. Children under 12years: ask a docto

Other information

Store at room temperature and out of directsunlight.

Inactive ingredients

Purified water, Artemisia extractsSophora Flavescens, Cnidium Monnieri (L.) Cuss., Kochiascoparia, Dictamni Cortex, Smilax Glabra Roxb, SolidagoDecurrens, Phellodendron amurense Ruprecht., GleditsiaSinensis.

When using this product avoid contact with eyeslf contact occurs, rinse the eves thoroughly with water.

QUESTIONS

Visit www.roycederm.com

Package Label - Principal Display Panel

81799-005-1

1

81799-005-1

2

81799-005-1

3